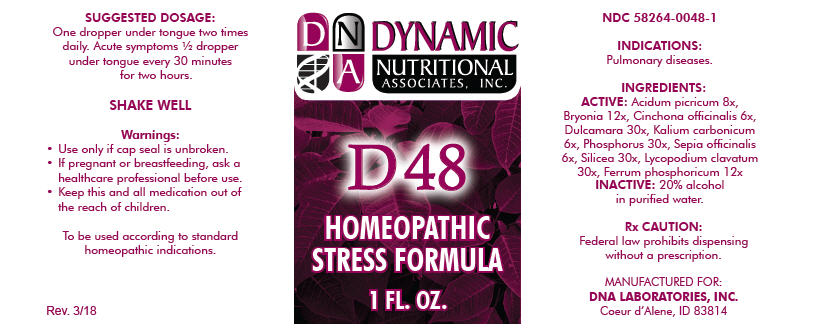 DRUG LABEL: D-48
NDC: 58264-0048 | Form: SOLUTION
Manufacturer: DNA Labs, Inc.
Category: homeopathic | Type: HUMAN OTC DRUG LABEL
Date: 20250113

ACTIVE INGREDIENTS: PICRIC ACID 8 [hp_X]/1 mL; BRYONIA ALBA ROOT 12 [hp_X]/1 mL; CINCHONA OFFICINALIS BARK 6 [hp_X]/1 mL; SOLANUM DULCAMARA WHOLE 30 [hp_X]/1 mL; POTASSIUM CARBONATE 6 [hp_X]/1 mL; PHOSPHORUS 30 [hp_X]/1 mL; SEPIA OFFICINALIS JUICE 6 [hp_X]/1 mL; SILICON DIOXIDE 30 [hp_X]/1 mL; LYCOPODIUM CLAVATUM SPORE 30 [hp_X]/1 mL; FERROSOFERRIC PHOSPHATE 12 [hp_X]/1 mL
INACTIVE INGREDIENTS: ALCOHOL; WATER

D-48

NDC 58264-0048-1

INDICATIONS

PURPOSE

Pulmonary diseases.

INGREDIENTS

ACTIVE

Acidum picricum 8x, Bryonia 12x, Cinchona officinalis 6x, Dulcamara 30x, Kalium carbonicum 6x, Phosphorus 30x, Sepia officinalis 6x, Silicea 30x, Lycopodium clavatum 30x, Ferrum phosphoricum 12x

INACTIVE

20% alcohol in purified water.

Rx CAUTION

Federal law prohibits dispensing without a prescription.

SUGGESTED DOSAGE

One dropper under tongue two times daily. Acute symptoms ½ dropper under tongue every 30 minutes for two hours.

STORAGE AND HANDLING

SHAKE WELL

Warnings

- Use only if cap seal is unbroken.

PREGNANCY OR BREAST FEEDING

- If pregnant or breastfeeding, ask a healthcare professional before use.

KEEP OUT OF REACH OF CHILDREN

- Keep this and all medication out of the reach of children.

To be used according to standard homeopathic indications.

PRINCIPAL DISPLAY PANEL - 1 FL. OZ. Bottle Label

DYNAMIC
NUTRITIONAL
ASSOCIATES, INC.

D 48

HOMEOPATHIC
STRESS FORMULA

1 FL. OZ.